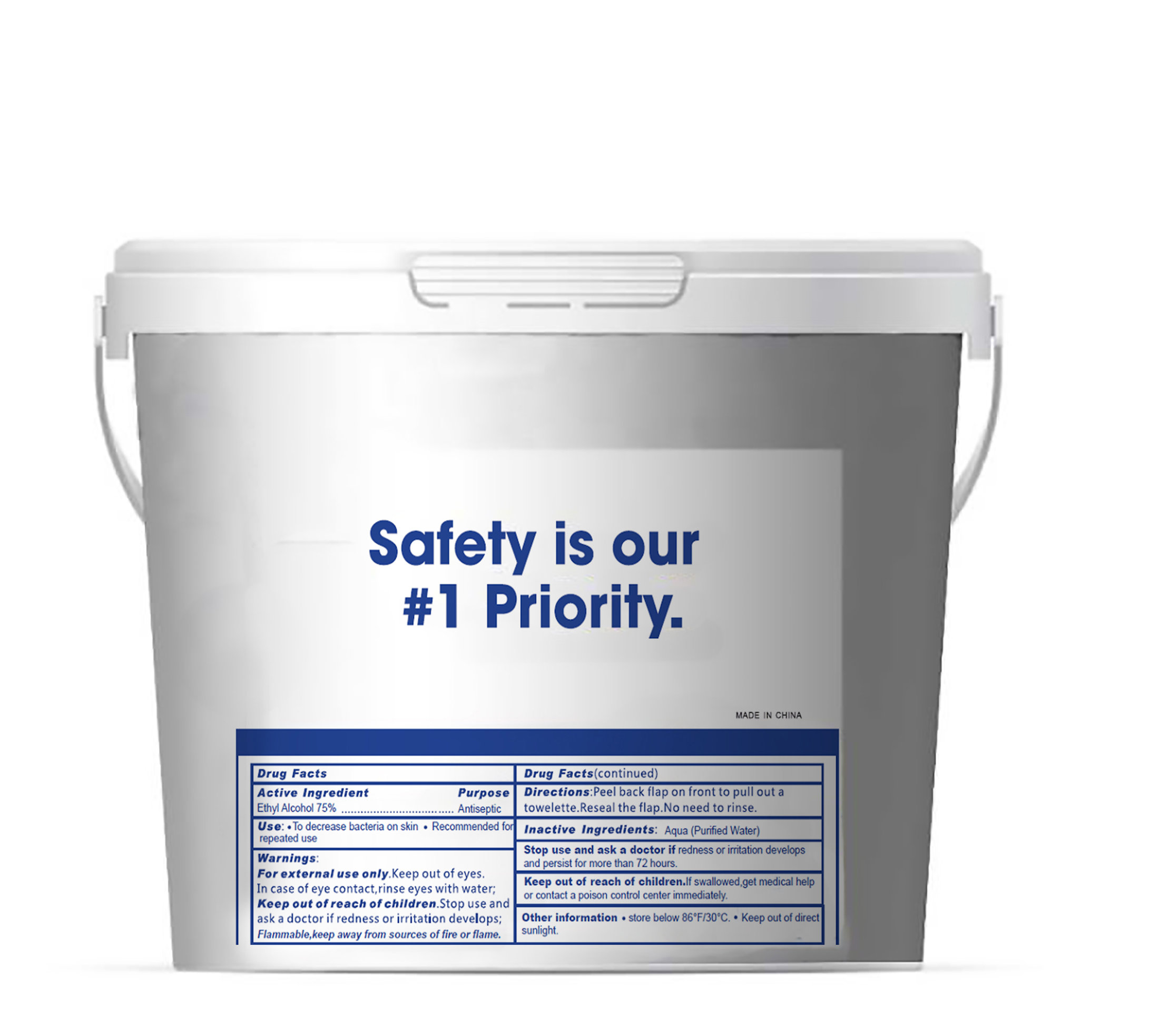 DRUG LABEL: sanitizing wipes
NDC: 42003-003 | Form: CLOTH
Manufacturer: Zhejiang jiayan daily commodity Co.,ltd
Category: otc | Type: HUMAN OTC DRUG LABEL
Date: 20200604

ACTIVE INGREDIENTS: ALCOHOL 0.75 mL/1 1
INACTIVE INGREDIENTS: WATER

sanitizing wipes

Active Ingredient(s)

Alcohol 75%. Purpose: Antiseptic

Purpose

Antiseptic

Use

- To decrease bacteria on skin.
- Recommended for repeated use

Warnings

For external use only.

Flmmable, keep away from sources of fire or flame.

When using this product

Keep our of eyes. In case of eye contact, rinse eyes with water

Stop use and ask a doctor if redness or irritation develops

Keep out of reach of children. If sallowed, get medical help or contact a poison control center immediately.

Directions

Peel back flap on front to pull out a towelette. Reseal the flap. No need to rinse.

Inactive ingredients

Aqua (Purified water)

Other information

- Store below 86F/30C.
- Keep out of direct sunlight.

Package Label - Principal Display Panel

400 PCS NDC: 42003-003-02